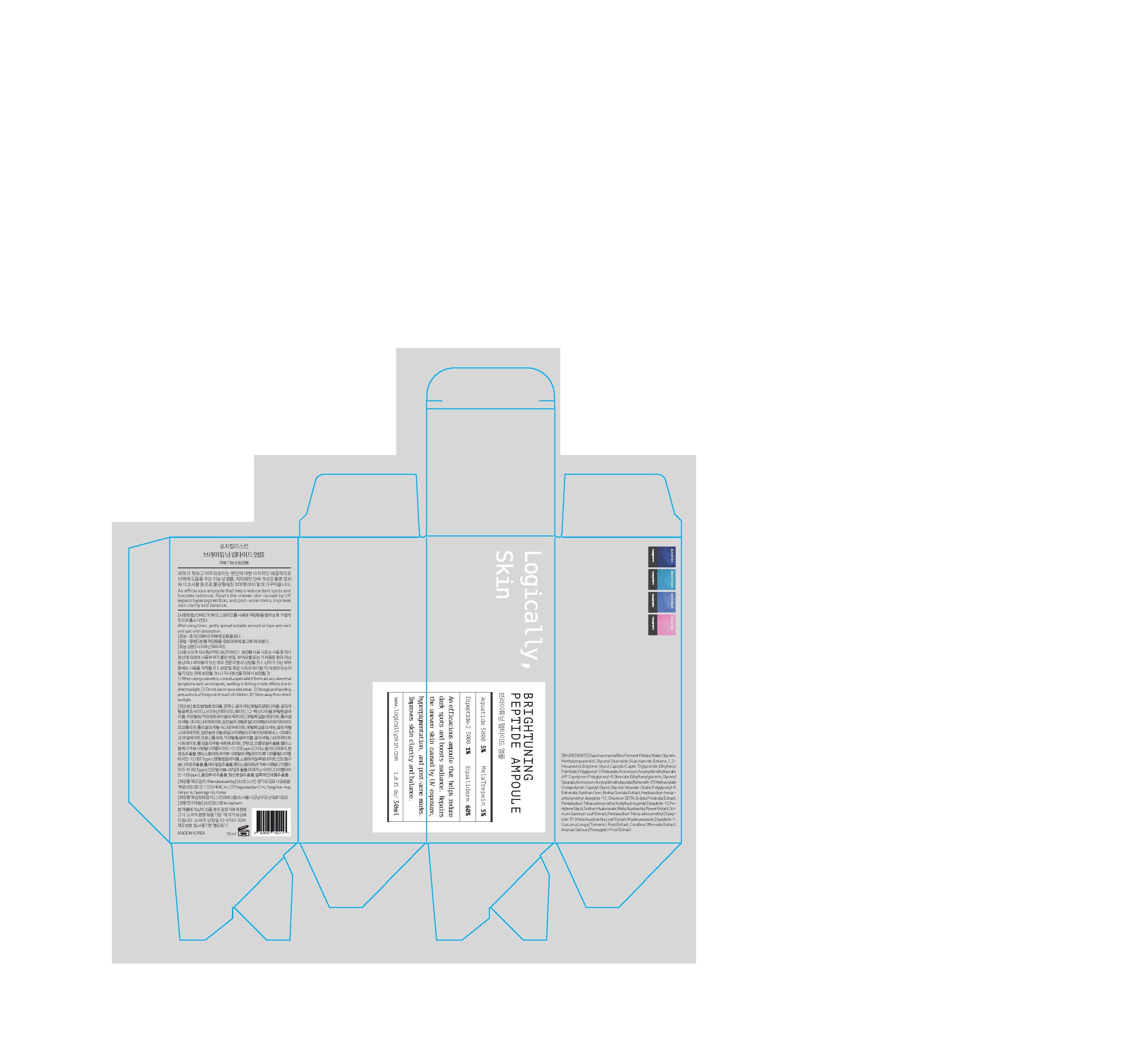 DRUG LABEL: BRIGHTUNING PEPTIDE AMPOULE
NDC: 73330-0002 | Form: LIQUID
Manufacturer: COSNINE, Inc.
Category: otc | Type: HUMAN OTC DRUG LABEL
Date: 20191223

ACTIVE INGREDIENTS: NIACINAMIDE 2 g/100 mL
INACTIVE INGREDIENTS: WATER; GLYCERIN

Drug Facts

ACTIVE INGREDIENT

niacinamide

INACTIVE INGREDIENT

Saccharomyces/Rice Ferment Filtrate
1,2-Hexanediol
Glyceryl Glucoside
Ananas Sativus (Pineapple) Fruit Extract
Butylene Glycol
Glycerin
Betaine
Disodium EDTA
Glyceryl Glucoside
Water
Glycerin
Methylpropanediol
Ammonium Acryloyldimethyltaurate/VP
Copolymer
Ammonium
Acryloyldimethyltaurate/Beheneth-25 Methacrylate Crosspolymer
Xanthan Gum
Polyglyceryl-6 Stearate
Polyglyceryl-6 Behenate
Caprylic/Capric Triglyceride
Polyglyceryl-3 Distearate
Glyceryl Stearate Citrate
Ethylhexylglycerin
Caprylyl Glycol
Ethylhexyl Palmitate
Glyceryl Stearate
Water
Butylene Glycol
1,2-Hexanediol
Sodium Hyaluronate
Glycerin
Water
Akebia Quinata Extract
1,2-Hexanediol
Water
Pentylene Glycol
Madecassoside
Melia Azadirachta Flower Extract
Ocimum Sanctum Leaf Extract
Melia Azadirachta Leaf Extract
Curcuma Longa (Turmeric) Root Extract
Corallina Officinalis Extract
Water
Eclipta Prostrata Extract
Water
Water
1,2-Hexanediol
Heptasodium Hexacarboxymethyl
Dipeptide-12
Water
1,2-Hexanediol
Pentasodium Tetracarboxymethyl
Acetylhydroxyprolyl Dipeptide-12
Pentasodium Tetracarboxymethyl
Dipeptide-51
Water
1,2-Hexanediol
Dipeptide-1

PURPOSE

helps skin whitening

keep out of reach of the children

INDICATIONS AND USAGE

apply proper amount to the skin

WARNINGS

1. Do not use in the following cases(Eczema and scalp wounds)
2.Side Effects
1)Due to the use of this druf if rash, irritation, itching and symptopms of hypersnesitivity occur dicontinue use and consult your phamacisr or doctor
3.General Precautions
1)If in contact with the eyes, wash out thoroughty with water If the symptoms are servere, seek medical advice immediately
2)This product is for exeternal use only. Do not use for internal use
4.Storage and handling precautions
1)If possible, avoid direct sunlight and store in cool and area of low humidity
2)In order to maintain the quality of the product and avoid misuse
3)Avoid placing the product near fire and store out in reach of children

DOSAGE AND ADMINISTRATION

for external use only